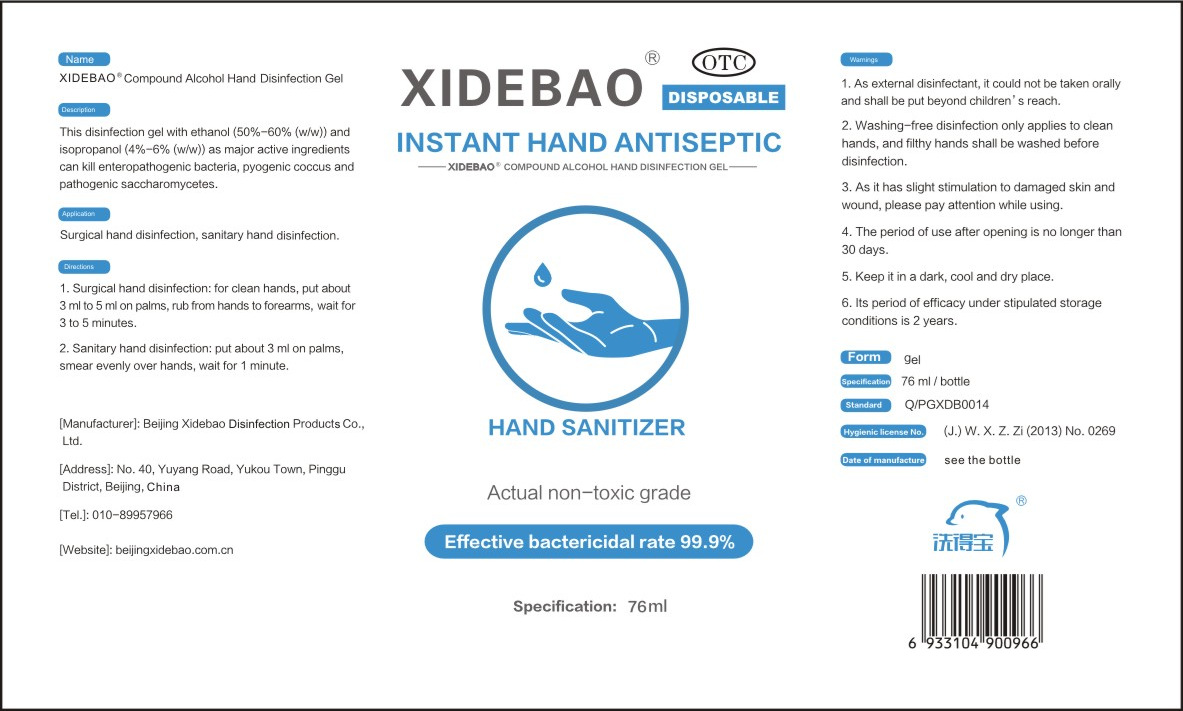 DRUG LABEL: Compound Alcohol Hand Disinfection Gel
NDC: 52779-001 | Form: GEL
Manufacturer: Beijing XiDeBao Disinfection Products Co. Ltd.
Category: otc | Type: HUMAN OTC DRUG LABEL
Date: 20200515

ACTIVE INGREDIENTS: ALCOHOL 45.6 mL/76 mL; ISOPROPYL ALCOHOL 4.56 mL/76 mL
INACTIVE INGREDIENTS: GLYCERIN; CARBOMER HOMOPOLYMER, UNSPECIFIED TYPE; WATER

DOSAGE AND ADMINISTRATION

Keep it in a dark, cooll and dry place.

INACTIVE INGREDIENT

Carbomer

purified water

glycerin

INDICATIONS AND USAGE

1. Surgical hand disinfection: for clean hands, put about 3 ml to 5 ml on palms, rub from hands to forearms, wait for 3 to 5 minutes.
2. Sanitary hand disinfection: put about 3 ml on palms,smear evenly over hands, wait for 1 minute.

ACTIVE INGREDIENT

Ethanol

isopropanol

keep out of reach of children

PURPOSE

Disinfection
Sterilization
No Rinseing

WARNINGS

1. As external disinfectant, it could not be taken orally and shall be put beyond children' s reach.
2. Washing-free disinfection only applies to clean hands, and fithy hands shall be washed before disinfection.
3. As it has slight stimulation to damaged skin and wound, please pay attention while using.
4. The period of use after opening is no longer than 30 days.
5. Keep it in a dark, cooll and dry place.
6. Its period of efficacy under stipulated storage conditions is 2 years.